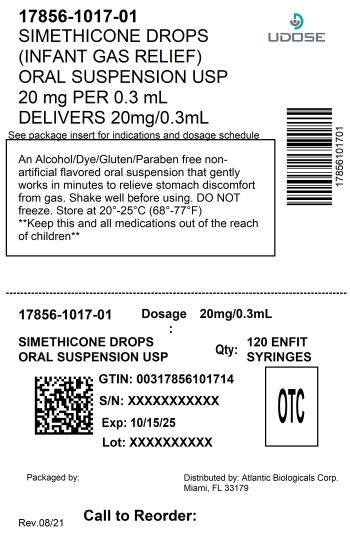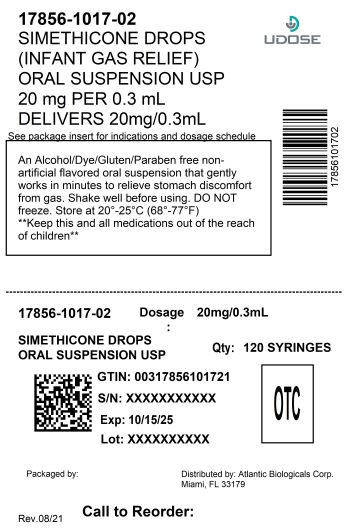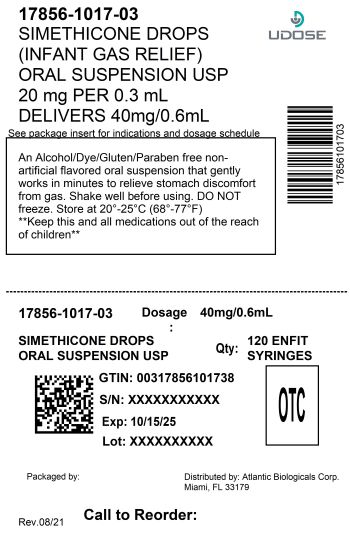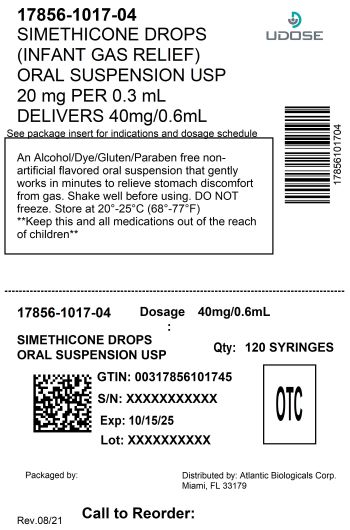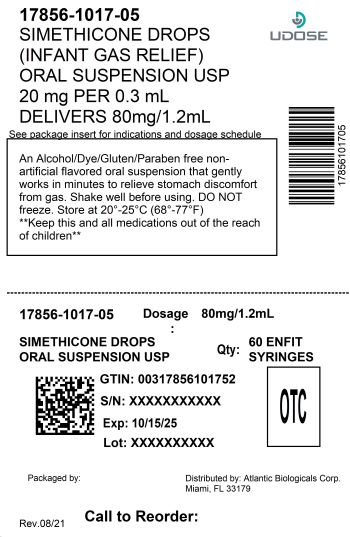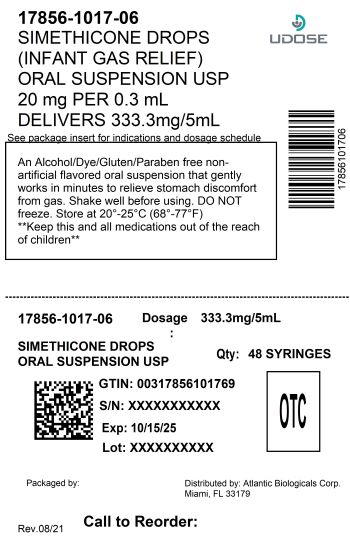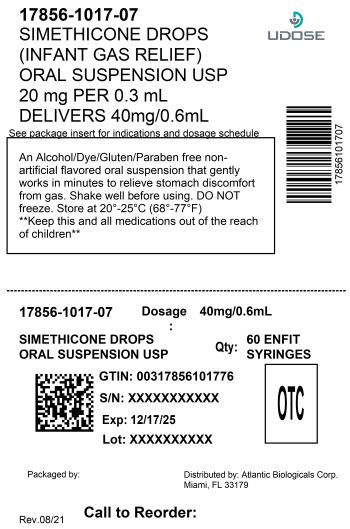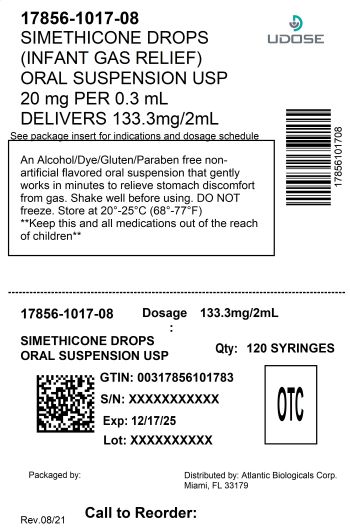 DRUG LABEL: SIMETHICONE INFANT
NDC: 17856-1017 | Form: SUSPENSION
Manufacturer: Atlantic Biologicals Corp.
Category: otc | Type: HUMAN OTC DRUG LABEL
Date: 20251217

ACTIVE INGREDIENTS: DIMETHICONE 20 mg/0.3 mL
INACTIVE INGREDIENTS: CARBOXYMETHYLCELLULOSE SODIUM, UNSPECIFIED FORM; ANHYDROUS CITRIC ACID; MICROCRYSTALLINE CELLULOSE; POLYSORBATE 60; POTASSIUM SORBATE; WATER; SODIUM BENZOATE; SORBITAN MONOSTEARATE; SORBITOL; XANTHAN GUM

SIMETHICONE INFANT GAS RELIEF DROPS
fast instant gas relief

Active ingredient (in each 0.3 mL)

Simethicone 20 mg

Purpose

Antigas

Uses

relieves the symptoms referred to as gas

Directions

- shake well before using
- all dosages may be repeated as needed, alter meals and at bedtime, or as directed by a physician
- do not exceed 12 doses per day
- fill enclosed dropper to recommended dosage level and dispense liquid slowly into baby's mouth, toward the inner cheek
- dosage can also be mixed with 1 oz. of cool water, infant formula or other suitable liquids

Age (years) | Weight (lbs) | Dose
infants (under 2) | under 24 | 0.3 mL
children (2 and over) | 24 and over | 0.6 mL

Other information

- TAMPER-EVIDENT:Do not use if printed seal under cap is broken or punctured
- store at room temperature
- do not freeze
- see bottom panel for lot number and expiration date

Inactive ingredients

Carboxymethylcellulose sodium, Citric acid, Flavor strawberry, Microcrystalline cellulose, Polysorbate 60, Potassium sorbate, Purified water, Sodium benzoate, Sorbitan monostearate, Sorbitol solution, Xanthan gum.

Questions or comments ?

Distributed by:

Atlantic Biologicals Corp.

Miami, FL 33179